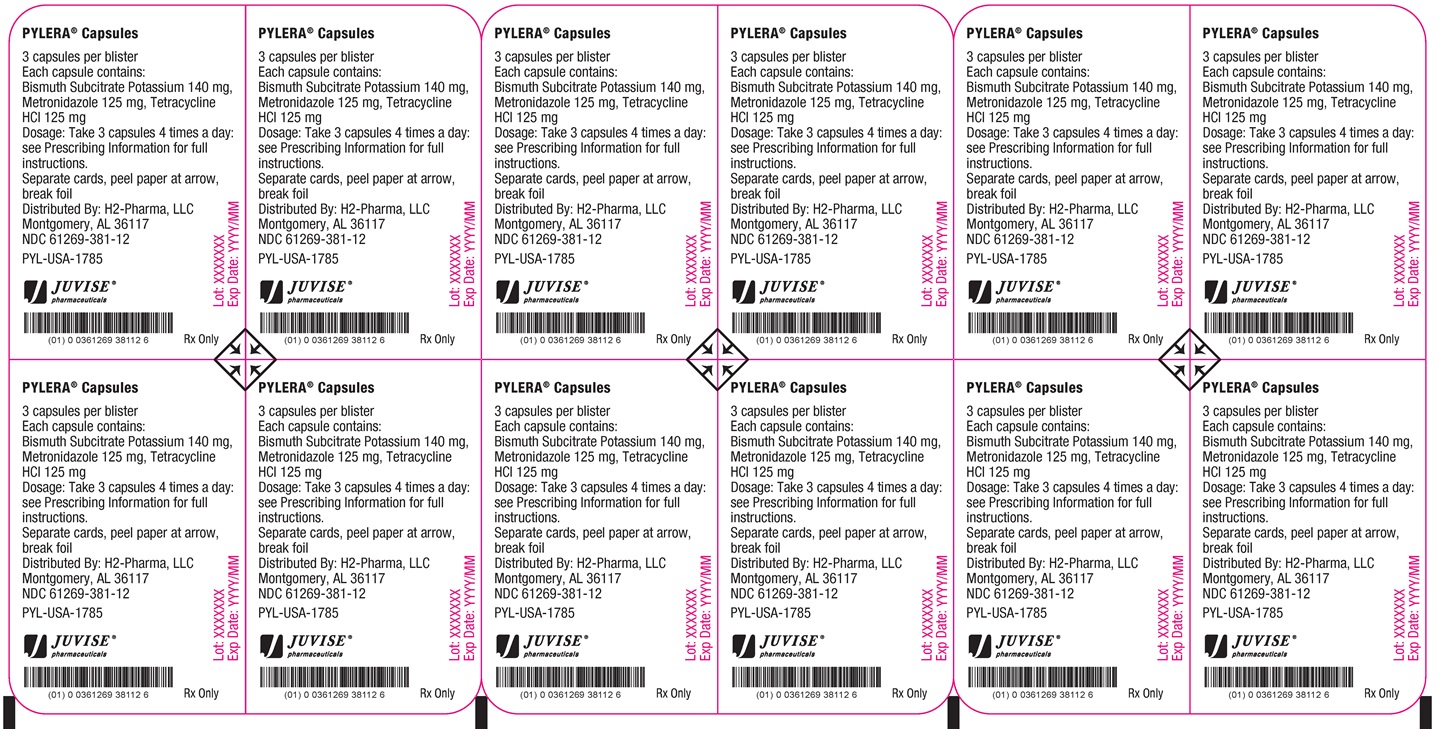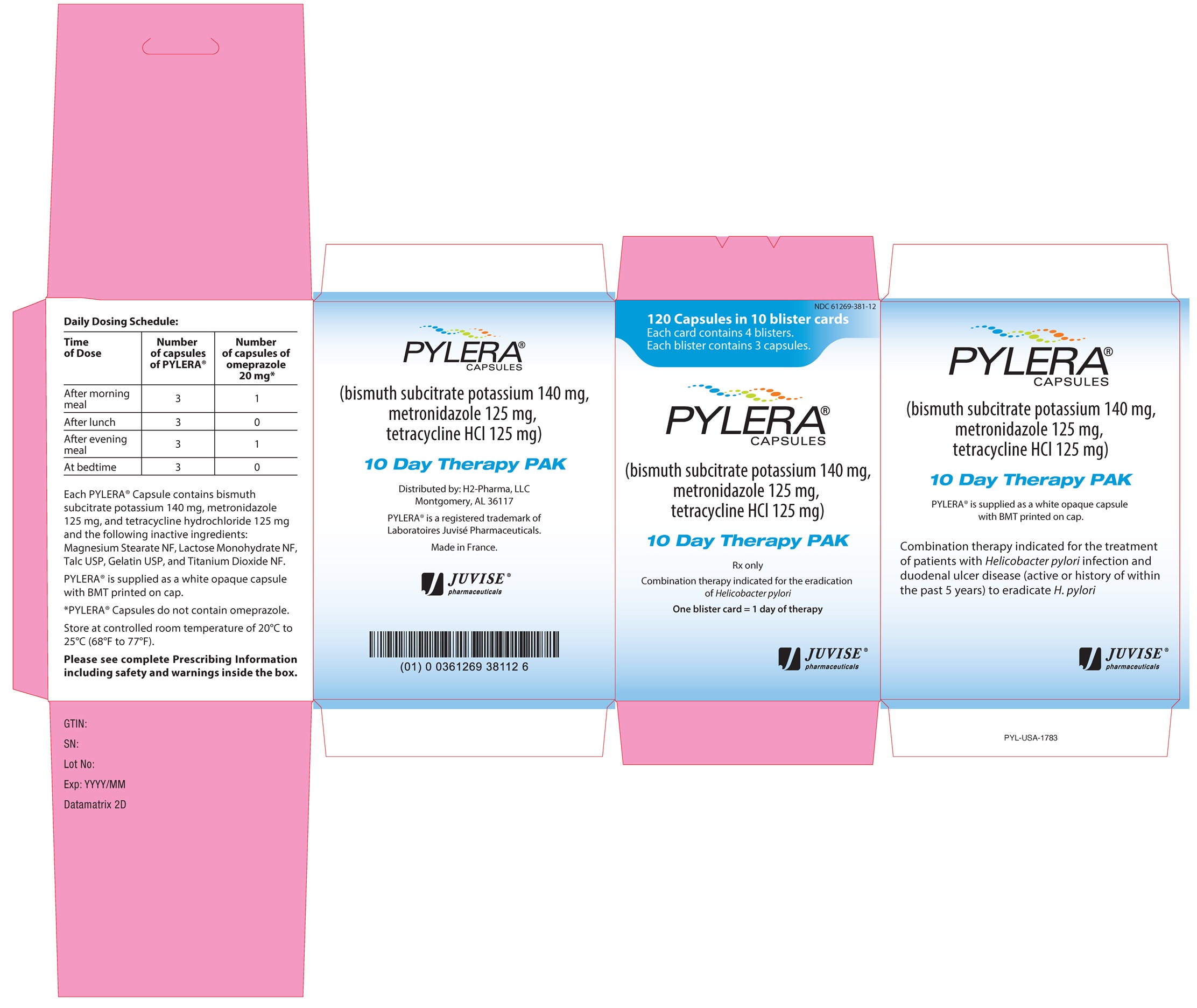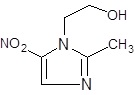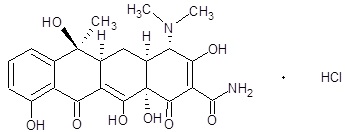 DRUG LABEL: PYLERA
NDC: 61269-381 | Form: CAPSULE
Manufacturer: H2-Pharma, LLC
Category: prescription | Type: HUMAN PRESCRIPTION DRUG LABEL
Date: 20260116

ACTIVE INGREDIENTS: BISMUTH SUBCITRATE POTASSIUM 140 mg/1 1; METRONIDAZOLE 125 mg/1 1; TETRACYCLINE HYDROCHLORIDE 125 mg/1 1
INACTIVE INGREDIENTS: MAGNESIUM STEARATE; LACTOSE MONOHYDRATE; TALC; GELATIN; TITANIUM DIOXIDE

HIGHLIGHTS OF PRESCRIBING INFORMATION

These highlights do not include all the information needed to use PYLERA safely and effectively. See full prescribing information for PYLERA.
PYLERA® (bismuth subcitrate potassium, metronidazole, tetracycline hydrochloride) capsules, for oral use
Initial U.S. Approval: 2006

WARNING: POTENTIAL FOR CARCINOGENICITY

See full prescribing information for complete boxed warning.

Metronidazole has been shown to be carcinogenic in mice and rats. It is unknown whether metronidazole is associated with carcinogenicity in humans (5.1).

RECENT MAJOR CHANGES

Warnings and Precautions, Severe Cutaneous Adverse Reactions (5.5) | 3/2025
Contraindications, Methoxyflurane (4.1) | Removed 3/2025

1 INDICATIONS AND USAGE

PYLERA is a combination of metronidazole, a nitroimidazole antimicrobial, tetracycline,- a tetracycline class antimicrobial and bismuth subcitrate potassium, indicated for use, in combination with omeprazole, for the treatment of patients with Helicobacter pylori infection and duodenal ulcer disease (active or history of within the past 5 years) to eradicate H. pylori. (1.1)
To reduce the development of drug-resistant bacteria and maintain the effectiveness of PYLERA and other antibacterial drugs, PYLERA should be used only to treat or prevent infections that are proven or strongly suspected to be caused by bacteria. (1.2)

2 DOSAGE AND ADMINISTRATION

- Administer three PYLERA capsules 4 times a day (after meals and at bedtime) for 10 days. (2)
- Administer PYLERA with omeprazole 20 mg twice daily (after the morning and evening meals). (2)

3 DOSAGE FORMS AND STRENGTHS

Each capsule of PYLERA contains: (3)

- 140 mg of bismuth subcitrate potassium
- 125 mg metronidazole
- 125 mg of tetracycline hydrochloride

4 CONTRAINDICATIONS

- Disulfiram usage within the last two weeks. (4.1, 7.1)
- Alcoholic beverage consumption for at least three days during or after therapy. (4.2, 7.2)
- Patients with Cockayne syndrome. (4.3, 6.3)
- Severe renal impairment. (4.4)
- Women who are pregnant. (4.5, 8.1)
- Known hypersensitivity to product components. (4.6)

5 WARNINGS AND PRECAUTIONS

- Fetal Toxicity: Advise pregnant women of the risk throughout pregnancy for retardation of skeletal development seen in animal studies and permanent discoloration of teeth with tetracycline if used during the second or third trimester. (5.2, 8.1)
- Maternal Toxicity: Risk of hepatotoxicity in pregnant women with high doses of intravenous tetracycline also resulting in stillborn or premature birth. (5.3, 8.1)
- Tooth Enamel discoloration and hypoplasia: permanent discoloration may develop with use during tooth development (last half of pregnancy, infancy, and childhood to the age of 8 years). (5.4)
- Severe Cutaneous Adverse Reactions: Severe cutaneous adverse reactions (SCARs) including toxic epidermal necrolysis (TEN), Stevens-Johnson syndrome (SJS), drug reaction with eosinophilia and systemic symptoms (DRESS), and acute generalized exanthematous pustulosis (AGEP) have been reported with metronidazole. If symptoms or signs of SCARs develop, discontinue PYLERA immediately and institute appropriate therapy. (5.5)
- Central and Peripheral Nervous System Effects: encephalopathy, convulsive seizures, aseptic meningitis and peripheral neuropathy with metronidazole, intracranial hypertension with tetracycline and neurotoxicity with bismuth-containing products. Monitor patients with CNS conditions closely and discontinue promptly if abnormal neurologic signs develop. (5.6)
- Photosensitivity: avoid exposure to sun and sun lamps. (5.8)
- Blood Dyscrasias: Use with caution in patients with a history of blood dyscrasias. (5.10)
- Hepatic Impairment: Not recommended in patients with severe hepatic impairment. (5.11)

6 ADVERSE REACTIONS

Most frequently reported adverse reactions (≥5%): abnormal feces, diarrhea, nausea, and headache. (6.1)
To report SUSPECTED ADVERSE REACTIONS, contact H2-Pharma, LLC at 1-833-520-8580 or FDA at 1-800-FDA-1088 or www.fda.gov/medwatch.

7 DRUG INTERACTIONS

- Disulfiram: Psychotic reactions can occur; do not take concurrently or within the last 2 weeks of disulfiram. (4.1, 7.1)
- Alcohol: Abdominal cramps, nausea, vomiting, headaches, and flushing can occur; do not consume during therapy and for at least 3 days afterwards. (4.2, 7.2)
- Oral Contraceptives: Decreased efficacy possibly resulting in pregnancy; use a different or additional form of contraception. (5.14, 7.3)
- Anticoagulants: Potentiation of the anticoagulant effect; Prothrombin time, International Normalized Ratio (INR), or other suitable anticoagulation tests should be closely monitored. (5.14, 7.4)
- Lithium: Increased lithium serum concentrations; measure serum lithium and serum creatinine concentrations during therapy. (5.14, 7.5)
- Antacids, Multivitamins or Dairy Products: Decreased absorption of PYLERA; do not take concomitantly. (7.6)
- Busulfan: Increased busulfan serum concentrations; avoid concomitant use, monitor for busulfan toxicity. (7.7)
- CYP inducers and CYP inhibitors: Prolonged or accelerated half-life of metronidazole or concomitant medications; use with caution. (7.8, 7.9)

8 USE IN SPECIFIC POPULATIONS

- Lactation: A woman should pump and discard human milk for the duration of PYLERA therapy, and for 2 days after therapy ends. (8.2)
- Pediatric Use: Tetracycline may cause permanent discoloration of the teeth. Enamel hypoplasia has also been reported. Do not use in children less than 8 years of age. (5.4, 8.4)

FULL PRESCRIBING INFORMATION

WARNING: POTENTIAL FOR CARCINOGENICITY

Metronidazole has been shown to be carcinogenic in mice and rats. It is unknown whether metronidazole is associated with carcinogenicity in humans [see Warning and Precautions (5.1)].

1 INDICATIONS AND USAGE

1.1 Eradication of Helicobacter pylori in Patients with Active Duodenal Ulcer or History of Duodenal Ulcer Disease

PYLERA in combination with omeprazole are indicated for the treatment of patients with Helicobacter pylori infection and duodenal ulcer disease (active or history of within the past 5 years) to eradicate H. pylori. The eradication of Helicobacter pylori has been shown to reduce the risk of duodenal ulcer recurrence.

1.2 Usage

To reduce the development of drug-resistant bacteria and maintain the effectiveness of PYLERA and other antibacterial drugs, PYLERA should be used to treat only indicated infections that are proven or strongly suspected to be caused by susceptible bacteria. When culture and susceptibility information are available, they should be considered in selecting or modifying antibacterial therapy. In the absence of such data, local epidemiology and susceptibility patterns may contribute to the empiric selection of therapy.

2 DOSAGE AND ADMINISTRATION

Administer three PYLERA capsules 4 times a day (after meals and at bedtime) for 10 days. One omeprazole 20 mg capsule should be taken twice a day with PYLERA after the morning and evening meal for 10 days (Table 1).

Table 1: Daily Dosing Schedule for PYLERA
Time of dose | Number of capsules of PYLERA | Number of capsules of omeprazole 20 mg
After morning meal | 3 | 1
After lunch | 3 | 0
After evening meal | 3 | 1
At bedtime | 3 | 0

Instruct patients to swallow the PYLERA capsules whole with a full glass of water (8 ounces). Ingestion of adequate amounts of fluid, particularly with the bedtime dose, is recommended to reduce the risk of esophageal irritation and ulceration by tetracycline hydrochloride.

If a dose is missed, patients should continue the normal dosing schedule until medication is gone. Patients should not take double doses. If more than 4 doses are missed, the prescriber should be contacted.

3 DOSAGE FORMS AND STRENGTHS

Each PYLERA capsule contains 140 mg of bismuth subcitrate potassium, 125 mg of metronidazole, and a smaller capsule inside containing 125 mg of tetracycline hydrochloride. The capsules are white and opaque, with “BMT” printed on the cap.

4 CONTRAINDICATIONS

4.1 Disulfiram

PYLERA is contraindicated in patients who have taken disulfiram within the last two weeks. Psychotic reactions have been reported in alcoholic patients who are using metronidazole, a component of PYLERA, and disulfiram concurrently [see Drug Interactions (7.1)].

4.2 Alcohol

Alcoholic beverages or other products containing propylene glycol should not be consumed during and for at least 3 days after therapy with PYLERA. A disulfiram-like reaction (abdominal cramps, nausea, vomiting, headaches, and flushing) may occur due to the interaction between alcohol or propylene glycol and metronidazole, a component of PYLERA [see Drug Interactions (7.2)].

4.3 Cockayne Syndrome

PYLERA is contraindicated in patients with Cockayne syndrome. Severe irreversible hepatotoxicity/acute liver failure with fatal outcomes have been reported after initiation of metronidazole in patients with Cockayne syndrome [see Adverse Reactions (6.3)].

4.4 Severe Renal Impairment

PYLERA is contraindicated in patients with severe renal impairment. The antianabolic action of the tetracyclines may cause an increase in blood urea nitrogen (BUN) [see Adverse Reactions (6.3)]. In patients with significantly impaired renal function, higher serum concentrations of tetracyclines may lead to azotemia, hyperphosphatemia, and acidosis.

4.5 Pregnancy

PYLERA is contraindicated during pregnancy [see Use in Specific Populations (8.1)].

4.6 Hypersensitivity Reactions

PYLERA is contraindicated in patients with known hypersensitivity (e.g. urticaria, erythematous rash, flushing, and fever) to bismuth subcitrate potassium, metronidazole or other nitroimidazole derivatives, or tetracycline [see Adverse Reactions (6.3)].

5 WARNINGS AND PRECAUTIONS

5.1 Potential for Carcinogenicity

Metronidazole, a component of PYLERA, has been shown to be carcinogenic in mice and rats. Tumors affecting the liver, lungs, mammary and lymphatic tissues have been detected in several studies of metronidazole in rats and mice, but not hamsters [see Nonclinical Toxicology (13)]. It is unknown whether metronidazole is associated with carcinogenicity in humans.

5.2 Fetal Toxicity

Tetracycline can cause fetal harm when administered to a pregnant woman. Based on animal data, use of drugs of the tetracycline class during the second and third trimester of pregnancy can cause permanent discoloration of the teeth (yellow-gray brown) and possibly inhibit bone development [see Warnings and Precautions (5.4)]. Administration of oral tetracycline to pregnant rats at various doses resulted in yellow fluorescence in teeth and bones in the newborn animals. If PYLERA is used during pregnancy, or if the patient becomes pregnant while taking PYLERA, advise the patient of the potential risk to the fetus [see Contraindications (4.5) and Use in Specific Populations (8.1)].

5.3 Maternal Toxicity

Tetracycline, a component of PYLERA, administered during pregnancy at high doses (> 2 g IV) was associated with rare but serious cases of maternal hepatotoxicity. This syndrome may result in stillborn or premature birth due to maternal pathology [see Contraindications (4.5) and Use in Specific Populations (8.1)].

5.4 Tooth Enamel Discoloration and Hypoplasia

The use of drugs of the tetracycline class during tooth development (last half of pregnancy, infancy, and childhood to the age of 8 years) may cause permanent discoloration of the teeth (yellow-gray-brown). This adverse reaction is more common during long-term use of the drug, but has been observed following repeated short-term courses. Enamel hypoplasia has also been reported. PYLERA, therefore, should not be used in this age group unless other drugs are not likely to be effective or are contraindicated [see Use in Specific Populations (8.4)].

5.5 Severe Cutaneous Adverse Reactions

Metronidazole: Severe cutaneous adverse reactions (SCARs) including toxic epidermal necrolysis (TEN), Stevens-Johnson syndrome (SJS), drug reaction with eosinophilia and systemic symptoms (DRESS), and acute generalized exanthematous pustulosis (AGEP) have been reported with the use of metronidazole. Symptoms can be serious and potentially life threatening. If symptoms or signs of SCARs develop, discontinue PYLERA capsules immediately and institute appropriate therapy.

Tetracycline: Fixed drug eruptions have occurred with tetracycline and have been associated with worsening severity upon subsequent administrations, including generalize bullous fixed drug eruption [see Adverse Reactions (6.3)]. If severe skin reactions occur, discontinue PYLERA immediately, and institute appropriate therapy.

5.6 Central and Peripheral Nervous System Effects

Metronidazole: Convulsive seizures, encephalopathy, aseptic meningitis and peripheral neuropathy (including optic neuropathy) have been reported. Encephalopathy has been reported in association with cerebellar toxicity characterized by ataxia, dizziness, and dysarthria. CNS lesions seen on MRI have been described in reports of encephalopathy. CNS symptoms are generally reversible within days to weeks upon discontinuation of metronidazole. CNS lesions seen on MRI have also been described as reversible. Peripheral neuropathy, mainly of sensory type has been reported and is characterized by numbness or paresthesia of an extremity. Aseptic meningitis symptoms may occur within hours of dose administration and generally resolve after metronidazole therapy is discontinued.

Tetracycline: Intracranial hypertension (IH), including pseudotumor cerebri, has been associated with the use of tetracyclines. Clinical manifestations of IH include headache, blurred vision, diplopia, and vision loss; papilledema can be found on fundoscopy. Women of childbearing age who are overweight or have a history of IH are at greater risk for developing tetracycline associated IH. Concomitant use of isotretinoin should be avoided because isotretinoin is also known to cause IH.

Although IH typically resolves after discontinuation of treatment, the possibility for permanent visual loss exists. If visual disturbance occurs during treatment, prompt ophthalmologic evaluation is warranted. Since intracranial pressure can remain elevated for weeks after drug cessation, patients should be monitored until they stabilize.

Bismuth-containing products: Cases of neurotoxicity associated with excessive doses of various bismuth-containing products have been reported. Effects have been reversible with discontinuation of bismuth therapy.

The appearance of abnormal neurologic signs and symptoms demands the prompt evaluation of the benefit/risk ratio of the continuation of PYLERA therapy [see Adverse Reactions (6.3)].

5.7 Development of Potential for Microbial Overgrowth

Known or previously unrecognized candidiasis may present more prominent symptoms during therapy with metronidazole and requires treatment with an antifungal agent. As with other antibacterial drugs, use of tetracycline hydrochloride may result in overgrowth of nonsusceptible organisms, including fungi. If superinfection occurs, discontinue PYLERA and institute appropriate therapy.

5.8 Photosensitivity

Photosensitivity, manifested by an exaggerated sunburn reaction, has been observed in patients taking tetracycline [see Adverse Reactions (6.3)]. Patients apt to be exposed to direct sunlight or ultraviolet light should be advised that this reaction can occur with tetracycline drugs. Instruct patients taking PYLERA to avoid exposure to the sun or sun lamps. Discontinue treatment at the first evidence of skin erythema.

5.9 Darkening of the Tongue and/or Black Stool

Bismuth subcitrate potassium may cause temporary and harmless darkening of the tongue and/or black stools, generally reversible within several days after treatment is stopped [see Adverse Reactions (6.1)]. Stool darkening should not be confused with melena.

5.10 Use in Patients with Blood Dyscrasias

Metronidazole is a nitroimidazole, and should be used with care in patients with evidence of or history of blood dyscrasia. A mild leukopenia has been observed during its administration; however, no persistent hematologic abnormalities attributable to metronidazole have been observed in clinical studies. Total and differential leukocyte counts are recommended before and after therapy [see Adverse Reactions (6.3)].

5.11 Increased Drug Plasma Concentrations in Patients with Hepatic Impairment

Patients with hepatic impairment metabolize metronidazole slowly, with resultant accumulation of metronidazole in the plasma. Patients with mild to moderate hepatic impairment should be monitored for metronidazole associated adverse events. PYLERA is not recommended in patients with severe hepatic impairment (Child-Pugh C) [see Clinical Pharmacology (12.3)].

5.12 Laboratory Test Interactions

Bismuth absorbs x-rays and may interfere with x-ray diagnostic procedures of the gastrointestinal tract.

Bismuth subcitrate potassium may cause a temporary and harmless darkening of the stool. However, this change does not interfere with standard tests for occult blood.

Metronidazole may interfere with certain types of determinations of serum chemistry values, such as aspartate aminotransferase (AST, SGOT), alanine aminotransferase (ALT, SGPT), lactate dehydrogenase (LDH), triglycerides, and hexokinase glucose. Values of zero may be observed. All of the assays in which interference has been reported involve enzymatic coupling of the assay to oxidation-reduction of nicotinamide (NAD+ <=> NADH). Interference is due to the similarity in absorbance peaks of NADH (340 nm) and metronidazole (322 nm) at pH 7.

5.13 Development of Drug Resistant Bacteria

Prescribing PYLERA in the absence of a proven or strongly suspected bacterial infection is unlikely to provide benefit to the patient and increases the risk of the development of drug-resistant bacteria.

5.14 Drug Interactions

Oral Contraceptives

Concurrent use of PYLERA with oral contraceptive may make oral contraceptives less effective due to an interaction with the tetracycline component of PYLERA. Breakthrough bleeding has been reported. Advise women of child-bearing potential to use a different or additional form of contraception while taking PYLERA [see Drug Interactions (7.3)].

Anticoagulants

PYLERA may alter the anticoagulant effects of warfarin and other oral coumarin anticoagulants. Metronidazole has been reported to potentiate the anticoagulant effect of warfarin, and other oral coumarin anticoagulants, resulting in a prolongation of prothrombin time. Tetracycline has been shown to depress plasma prothrombin activity. Closely monitor prothrombin time, International Normalized Ratio (INR), or other suitable anticoagulation tests if PYLERA is administered concomitantly with warfarin. Patients should also be monitored for evidence of bleeding [see Drug Interactions (7.4)].

Lithium

In patients stabilized on relatively high doses of lithium, short-term use of PYLERA may cause elevation of serum lithium concentrations and signs of lithium toxicity due to the interaction between metronidazole and lithium. Monitor serum lithium and serum creatinine concentrations daily for several days after beginning treatment with PYLERA to detect any increase that may precede clinical symptoms of lithium toxicity [see Drug Interactions (7.5)].

Busulfan

Metronidazole has been reported to increase plasma concentrations of busulfan, which can result in an increased risk for serious busulfan toxicity. Do not administer PYLERA concomitantly with busulfan unless the benefit outweighs the risk. If no therapeutic alternatives to PYLERA are available, and concomitant administration with busulfan is medically needed, monitor for busulfan toxicity and busulfan plasma concentrations and adjust the busulfan dose accordingly [see Drug Interactions (7.7)].

Drugs that Prolong the QT interval

QT prolongation has been reported with metronidazole, a component of PYLERA, particularly when administered with drugs with the potential for prolonging the QT interval.

6 ADVERSE REACTIONS

6.1 Clinical Trials Experience

Because clinical trials are conducted under widely varying conditions, adverse reaction rates observed in the clinical trials of a drug cannot be directly compared to rates in the clinical trials of another drug and may not reflect the rates observed in practice.

The safety of PYLERA plus omeprazole (OBMT) to eradicate Helicobacter pylori was assessed in an open-label, randomized, active-controlled clinical trial conducted in North America. The duration of treatment was 10 days with 147 patients exposed to PYLERA plus omeprazole (OBMT) and 152 exposed to control, consisting of omeprazole, amoxicillin, and clarithromycin (OAC). The age of the population in the study ranged from 18 to 75 years, with 59% male patients and 59% Caucasian patients.

Adverse drug reactions were reported in 58% of patients in the OBMT group and 59% of patients in the OAC group. There were no adverse reactions leading to discontinuation of the study during the clinical trial.

Adverse reactions with an incidence of ≥ 5% in OBMT group include abnormal feces, diarrhea, nausea, and headache. Adverse drug reactions with an incidence of ≥ 5% in OAC group include diarrhea, dysgeusia, dyspepsia, nausea and headache.

Table 2 lists adverse reactions with an incidence of ≥ 1%, in either group (OBMT vs OAC) and in order of decreasing incidence for the OBMT group.

Table 2: Adverse reactions with an incidence of ≥ 1% from North American trial, [n (%)]
Preferred Term | OBMT* (n = 147) | OAC** (n = 152)
Gastrointestinal disorders
Abnormal feces*** | 23 (15.6%) | 7 (4.6%)
Nausea | 12 (8.2%) | 14 (9.2%)
Diarrhea | 10 (6.8%) | 20 (13.2%)
Abdominal Pain | 7 (4.8%) | 2 (1.3%)
Dyspepsia | 4 (2.7%) | 10 (6.6%)
Constipation | 2 (1.4%) | 5 (3.3%)
Dry Mouth | 2 (1.4%) | 1 (0.7%)
Flatulence | 0 | 4 (2.6%)
Glositis | 0 | 2 (1.3%)
General disorders and administration site conditions
Asthenia | 5 (3.4%) | 2 (1.3%)
Infections and infestations
Vaginal infection | 4 (2.7%) | 3 (2.0%)
Nervous system disorders
Headache | 8 (5.4%) | 8 (5.3%)
Dysgeusia | 6 (4.1%) | 18 (11.8%)
Dizziness | 4 (2.7%) | 4 (2.6%)
Investigations
Laboratory test abnormal | 3 (2.0%) | 4 (2.6%)
Alanine aminotransferase increased | 2 (1.4%) | 0
Aspartate aminotransferase increased | 2 (1.4%) | 0
Renal and urinary disorders
Urine abnormality | 2 (1.4%) | 0
Skin and subcutaneous tissue disorders
Rash Maculo-Papular | 2 (1.4%) | 0
Rash | 1 (0.7%) | 3 (2.0%)
Pruritus | 0 | 4 (2.6%)

*OBMT = Omeprazole + PYLERA

**OAC = Omeprazole + Amoxicillin + Clarithromycin;

*** Dark stools [see Warnings and Precautions (5.9)]

Adverse reactions with an incidence of <1% for OBMT group are: back pain, vomiting, tongue darkening [see Warnings and Precautions (5.9)], anxiety, gastritis, gastroenteritis, myalgia, chest pain, increased appetite, blood creatine phosphokinase increased, malaise, somnolence, tachycardia, duodenal ulcer, visual disturbance, weight increased.

6.2 Postmarketing Experience

Additionally, the following adverse reactions, presented by system organ class in alphabetical order, have been identified during post approval use of PYLERA. Because these reactions are reported voluntarily from a population of uncertain size, it is not always possible to reliably estimate their frequency or establish a causal relationship to drug exposure.

- Gastrointestinal disorders: abdominal distention, eructation, flatulence
- General disorders and administration site conditions: chest discomfort, fatigue
- Infections and infestations: candidiasis, pseudomembranous colitis (Clostridium difficile colitis)
- Nervous Systems: peripheral neuropathy
- Skin and subcutaneous disorders: Stevens-Johnson syndrome, toxic epidermal necrolysis, DRESS syndrome (drug rash with eosinophilia and systemic symptoms) [see Warnings and Precautions (5.5)]

6.3 Other Important Adverse Reactions from Labeling for the Individual Components of PYLERA

Metronidazole

Blood and Lymphatic system disorders: Reversible neutropenia (leucopenia) in cases of prolonged treatment; rarely reversible thrombocytopenia however no persistent hematological abnormalities attributable to metronidazole have been observed [see Warnings and Precautions (5.10)].

Cardiac disorders: QT prolongation has been reported with metronidazole, particularly when administered with drugs with the potential for prolonging the QT interval. Flattening of the T-wave may be seen in electrocardiographic tracings.

Gastrointestinal disorders: Nausea, vomiting, diarrhea, abdominal pain, constipation, anorexia, metallic taste, furry tongue, glossitis, stomatitis and candida overgrowth.

Hypersensitivity/Immune system disorders: Acute generalized exanthematous pustulosis (AGEP) [see Warnings and Precautions (5.5)], urticaria, erythematous rash, flushing, nasal congestion, dryness of the mouth (or vagina or vulva), and fever [see Contraindications (4.6)].

Metabolism and nutrition disorders: Pancreatitis.

Nervous system disorders: Convulsive seizures, encephalopathy, aseptic meningitis, optic and peripheral neuropathy, headache, syncope, dizziness, vertigo, incoordination, ataxia, tinnitus, hearing impairment, hearing loss, confusion, dysarthria, irritability, depression, weakness, and insomnia [see Warnings and Precautions (5.6)].

Dermatologic disorders: Erythematous rash and pruritus.

Renal and urinary disorders: Dysuria, cystitis, polyuria, incontinence, darkened urine, and a sense of pelvic pressure.

Hepatic: Cases of severe irreversible hepatotoxicity/acute liver failure, including cases with fatal outcomes with very rapid onset after initiation of systemic use of metronidazole, have been reported in patients with Cockayne Syndrome (latency from drug start to signs of liver failure as short as 2 days) [see Contraindications (4.3)].

Other: Dyspareunia, decrease of libido, proctitis, joint pains.

Tetracycline Hydrochloride

Blood and lymphatic system disorders: Hemolytic anemia, thrombocytopenia, thrombocytopenic purpura, neutropenia, and eosinophilia.

Gastrointestinal disorders: Nausea, vomiting, diarrhea, anorexia, glossitis, black hairy tongue, dysphagia, enterocolitis, inflammatory lesions (with Candida overgrowth) in the anogenital region, esophagitis and esophageal ulceration.

Nervous system disorders: Intracranial hypertension including pseudotumor cerebri, tinnitus, and myasthenic syndrome.

Renal and urinary disorders: Increased BUN.

Skin and subcutaneous tissue disorders: Maculopapular and erythematous rashes, onycholysis, fixed drug eruption, discoloration of the nails, exfoliative dermatitis and photosensitivity have been rarely reported [see Warnings and Precautions (5.8)].

Liver: Hepatotoxicity and liver failure.

Hypersensitivity reactions: Urticaria, angioedema, anaphylaxis, Henoch-Schonlein purpura, pericarditis, exacerbation of systemic lupus erythematosus, and serum sickness-like reactions.

7 DRUG INTERACTIONS

7.1 Disulfiram

Psychotic reactions have been reported in alcoholic patients who are using metronidazole, a component of PYLERA and disulfiram concurrently. PYLERA should not be given to patients who have taken disulfiram within the last two weeks [see Contraindications (4.1)].

7.2 Alcohol

Consumption of alcoholic beverages or administration of other products containing propylene glycol during treatment with PYLERA and for at least 3 days afterwards may cause a disulfiram-like reaction (abdominal cramps, nausea, vomiting, headaches, and flushing) due to the interaction between alcohol or propylene glycol and metronidazole, a component of PYLERA. Discontinue alcoholic beverage or other products containing propylene glycol during and for at least 3 days after therapy with PYLERA [see Contraindications (4.2)].

7.3 Oral Contraceptives

Concurrent use of PYLERA with oral contraceptive may make oral contraceptives less effective due to an interaction with the tetracycline component of PYLERA. Breakthrough bleeding has been reported. Women of child-bearing potential should use a different or additional form of contraception while taking PYLERA [see Warnings and Precautions (5.14)].

7.4 Anticoagulants

PYLERA may alter the anticoagulant effects of warfarin and other oral coumarin anticoagulants. Metronidazole has been reported to potentiate the anticoagulant effect of warfarin, and other oral coumarin anticoagulants, resulting in a prolongation of prothrombin time. Tetracycline has been shown to depress plasma prothrombin activity. Prothrombin time, International Normalized Ratio (INR), or other suitable anticoagulation tests should be closely monitored if PYLERA is administered concomitantly with warfarin. Patients should also be monitored for evidence of bleeding [see Warnings and Precautions (5.14)].

7.5 Lithium

In patients stabilized on relatively high doses of lithium, short-term use of PYLERA may cause elevation of serum lithium concentrations and signs of lithium toxicity due to the interaction between metronidazole and lithium. Serum lithium and serum creatinine concentrations should be monitored several days after beginning treatment with PYLERA to detect any increase that may precede clinical symptoms of lithium toxicity [see Warnings and Precautions (5.14)].

7.6 Antacids, Multivitamins, or Dairy Products

The absorption of PYLERA may be reduced if administered with antacids containing aluminium, calcium, or magnesium; preparations containing iron, zinc, or sodium bicarbonate; or milk or dairy products due to the interaction between these products and tetracycline. These products should not be consumed concomitantly with PYLERA. However, the clinical significance of reduced tetracycline systemic exposure is unknown as the relative contribution of systemic versus local antimicrobial activity against Helicobacter pylori has not been established.

7.7 Busulfan

Metronidazole has been reported to increase plasma concentrations of busulfan, which can result in an increased risk for serious busulfan toxicity. Do not administer PYLERA concomitantly with busulfan unless the benefit outweighs the risk. If no therapeutic alternatives to PYLERA are available, and concomitant administration with busulfan is medically needed, monitor for busulfan toxicity and busulfan plasma concentrations and adjust the busulfan dose accordingly [see Warnings and Precautions (5.14)].

7.8 Inhibitors of CYP450 liver enzymes

The simultaneous administration of PYLERA and drugs that inhibit microsomal liver enzymes, such as cimetidine, may result in a prolonged half-life and decreased plasma clearance of metronidazole.

7.9 Inducers of CYP450 liver enzymes

The simultaneous administration of PYLERA and drugs that induce microsomal liver enzymes, such as phenytoin or phenobarbital, may accelerate the elimination of metronidazole, resulting in reduced plasma concentrations of metronidazole. Impaired clearance of phenytoin has also been reported in this situation. Monitor phenytoin concentrations during treatment with PYLERA.

8 USE IN SPECIFIC POPULATIONS

8.1 Pregnancy

Risk Summary

PYLERA is contraindicated in women who are pregnant because treatment of Helicobacter pylori infection can be delayed in pregnant women, and the use of drugs of the tetracycline class during the second and third trimester pregnancy can also cause permanent discoloration of the teeth (yellow-gray brown) and possibly inhibit bone development [see Warnings and Precautions (5.2) and Data]. Administration of oral tetracycline to pregnant rats at various doses resulted in yellow fluorescence in teeth and bones in the newborn animals. There are maternal risks with high intravenous doses of tetracycline [see Clinical Considerations].

Metronidazole usage in pregnancy has been associated with certain congenital anomalies [see Data]. In animals, no fetotoxicity was observed when metronidazole was orally administered to pregnant mice at approximately 5% of the indicated human dose. There are no human or animal data on the use of bismuth subcitrate potassium during pregnancy. Although there are data on the separate components, there are no available data on the use of PYLERA in pregnant women.

Clinical Considerations

Maternal Adverse Reactions

Tetracycline administered during pregnancy at high doses (> 2 g IV) was associated with rare but serious cases of maternal hepatotoxicity. This syndrome may result in stillborn or premature birth due to maternal pathology [see Warnings and Precautions (5.3)].

Data

Human Data

Tetracycline

Published case reports have described the yellowing of bones and teeth in human infants exposed to tetracycline during the second and third trimester of pregnancy. The yellowing is caused by the direct deposition of tetracycline during the mineralization process. This discoloration is more common during long-term use of the drug but has also been observed following repeated short-term courses. All tetracyclines form a stable calcium complex in any bone forming tissue. A decrease in fibula growth rate was observed in premature infants given oral tetracycline in doses of 25 mg/kg every six hours. The effect resolved when the drug was discontinued. One long-term follow-up study in children exposed to tetracycline in-utero showed no adverse effects on bone growth and development.

Metronidazole

There are published data from case-control studies, cohort studies, and 2 meta-analyses that include more than 5000 pregnant women who used metronidazole during pregnancy. Many studies included first trimester exposures. One study showed an increased risk of cleft lip, with or without cleft palate, in infants exposed to metronidazole in-utero; however, these findings were not confirmed. In addition, more than ten randomized, placebo-controlled clinical trials enrolled more than 5000 pregnant women to assess the use of antibiotic treatment (including metronidazole) for bacterial vaginosis on the incidence of preterm delivery. Most studies did not show an increased risk for congenital anomalies or other adverse fetal outcomes following metronidazole exposure during pregnancy. Three studies conducted to assess the risk of infant cancer following metronidazole exposure during pregnancy did not show an increased risk; however, the ability of these studies to detect such a signal was limited.

Bismuth subcitrate potassium

There are no human data on the use of bismuth subcitrate potassium during pregnancy.

Animal Data

Tetracycline

Results of animal studies indicate that tetracycline crosses the placenta, is found in fetal tissues, and can have toxic effects on the developing fetus (often related to reversible retardation of skeletal development). Evidence of embryotoxicity has also been noted in animals treated early in pregnancy. Multiple studies of limited design were conducted with pregnant and lactating female rats that resulted in fetuses and neonates with yellow discoloration of bones and teeth.

Metronidazole

Metronidazole crosses the placental barrier. No fetotoxicity was observed when metronidazole was administered orally to pregnant mice at 10 mg/kg/day, approximately 5 percent of the indicated human dose (1500 mg/day) based on body surface area; however in a single small study where the drug was administered intraperitoneally, some intrauterine deaths were observed. The relationship of these findings to the drug is unknown.

Bismuth subcitrate potassium

Animal reproductive studies have not been conducted with bismuth subcitrate potassium.

8.2 Lactation

Risk Summary

Two of the individual components of PYLERA, tetracycline and metronidazole, are present in human milk at concentrations similar to maternal serum levels. It is not known whether bismuth subcitrate, the third component of PYLERA is present in human milk. It is not known what effect metronidazole, tetracycline or bismuth has on the breastfed infant or on milk production. Tetracycline binds with calcium in human milk [see Clinical Pharmacology (12.3)]. Data indicate that oral absorption of tetracycline in infants is low due to the calcium binding in human milk. Metronidazole transfers to human milk, and infant serum levels can be close to or comparable to infant therapeutic levels. Because of the potential risk of tumorigenicity shown in animal studies with metronidazole, a woman should pump and discard human milk for the duration of PYLERA therapy, and for 2 days after therapy ends, and feed her infant stored human milk (collected prior to therapy) or formula.

8.4 Pediatric Use

Safety and effectiveness of PYLERA in pediatric patients infected with Helicobacter pylori have not been established.

Tetracycline use in children may cause permanent discoloration of the teeth. Enamel hypoplasia has also been reported. PYLERA should not be used in children up to 8 years of age [see Warnings and Precaution (5.4)].

8.5 Geriatric Use

Clinical studies of PYLERA did not include sufficient numbers of patients aged 65 and over to determine whether they respond differently than younger patients. Other reported clinical experience has not identified differences in responses between the elderly and younger patients. In general, elderly patients may have a greater frequency of decreased hepatic, renal, or cardiac function, and concomitant diseases or other drug therapies. Bismuth subcitrate potassium, a component of PYLERA, is known to be substantially excreted by the kidney, and the risk of adverse reactions may be greater in patients with impaired renal function. Because elderly patients are more likely to have decreased renal function, additional monitoring may be required [see Contraindications (4.4)].

8.6 Renal Impairment

The antianabolic action of the tetracyclines may cause an increase in blood urea nitrogen (BUN). In patients with severe renal impairment, higher serum concentrations of tetracycline may lead to azotemia, hyperphosphatemia, and acidosis [see Contraindications (4.4)].

8.7 Hepatic Impairment

Patients with severe hepatic disease metabolize metronidazole slowly, with resultant accumulation of metronidazole and its metabolites in plasma. Patients with mild to moderate hepatic impairment should be monitored for metronidazole associated adverse events. PYLERA is not recommended in patients with severe hepatic impairment [see Warnings and Precautions (5.11) and Clinical Pharmacology (12.3)].

10 OVERDOSAGE

In case of an overdose, patients should contact a physician, poison control center, or emergency room. The available overdosage information for each of the individual components in PYLERA (Metronidazole, Tetracycline and Bismuth subcitrate potassium) are summarized below:

Metronidazole:

Single oral doses of metronidazole, up to 15 g, have been reported in suicide attempts and accidental overdoses. Symptoms reported include nausea, vomiting, and ataxia. Metronidazole is dialyzable.

Neurotoxic effects, including seizures and peripheral neuropathy, have been reported after 5 to 7 days of doses of 6 to 10.4 g every other day.

Treatment of Overdosage

There is no specific antidote for metronidazole overdose; therefore, management of the patient should consist of symptomatic and supportive therapy.

Tetracycline:

In case of overdosage, discontinue medication, treat symptomatically and institute supportive measures. Dialysis does not alter serum half-life and thus would not be of benefit in treating cases of overdosage.

Bismuth subcitrate potassium:

Symptoms of a bismuth subcitrate potassium overdosage are not known.

11 DESCRIPTION

PYLERA capsules are a combination antimicrobial product containing bismuth subcitrate potassium, metronidazole, and tetracycline hydrochloride for oral administration. Each size 0 elongated capsule contains:

- bismuth subcitrate potassium, 140 mg
- metronidazole, 125 mg
- smaller capsule (size 3) containing tetracycline hydrochloride, 125 mg

Tetracycline hydrochloride is encapsulated within a smaller capsule to create a barrier to avoid contact with bismuth subcitrate potassium.

Each PYLERA capsule contains the following inactive ingredients: Magnesium Stearate NF, Lactose Monohydrate NF, Talc USP, Gelatin USP, and Titanium Dioxide NF, Printed in red ink.

Bismuth subcitrate potassium is a white or almost white powder. It is a soluble, complex bismuth salt of citric acid. The schematized empirical molecular formula of bismuth subcitrate potassium is Bi (Citrate)2K5●3 H2O. The equivalent theoretical molecular formula is BiC12H14K5O17. The molecular mass of the theoretical molecular formula of a single unit of bismuth subcitrate potassium is 834.71.

Metronidazole is a white to pale yellow crystalline powder. Metronidazole is 2-methyl-5-nitroimidazole-1-ethanol, with a molecular
formula of C6H9N3O3 and the following structural formula:

Molecular weight: 171.2

Tetracycline hydrochloride is a yellow, odorless, crystalline powder. Tetracycline hydrochloride is stable in air, but exposure to strong sunlight causes it to darken. Tetracycline hydrochloride is (4S,4aS,5aS,6S,12aS)-4-(dimethylamino)-1,4,4a,5,5a,6,11,12a-octahydro-3,6,10,12,12a-penta-hydroxy-6-methyl-1,11-dioxo-2-naphthacenecarboxamide hydrochloride, with a molecular formula of C22H24N2O8●HCl and the following structural formula:

Molecular weight: 480.90

12 CLINICAL PHARMACOLOGY

12.1 Mechanism of Action

PYLERA is a combination of antibacterial agents (metronidazole and tetracycline hydrochloride) and bismuth subcitrate potassium [see Microbiology (12.4)].

12.3 Pharmacokinetics

The pharmacokinetics of the individual components of PYLERA, bismuth subcitrate potassium, metronidazole and tetracycline hydrochloride are summarized below. In addition, two studies on PYLERA were conducted to determine the effect of co-administration on the pharmacokinetics of the components.

Bismuth Subcitrate Potassium (Bismuth)

Absorption and Distribution

Orally absorbed bismuth is distributed throughout the entire body. Bismuth is highly bound to plasma proteins (>90%).

Metabolism and Excretion

The elimination half-life of bismuth is approximately 5 days in both blood and urine. Elimination of bismuth is primarily through urinary and biliary routes. The rate of renal elimination appears to reach steady state 2 weeks after treatment discontinuation with similar rates of elimination at 6 weeks after discontinuation. The average urinary elimination of bismuth is 2.6% per day in the first two weeks after discontinuation (urine drug concentrations 24 to 250 mcg/mL) suggesting tissue accumulation and slow elimination.

Metronidazole

Absorption and Distribution

Following oral administration, metronidazole is well absorbed, with peak plasma concentrations occurring between 1 and 2 hours after administration. Plasma concentrations of metronidazole are proportional to the administered dose, with oral administration of 500 mg producing a peak plasma concentration of 12 mcg/mL.

Metronidazole appears in the plasma mainly as unchanged compound with lesser quantities of the 2-hydroxymethyl metabolite also present. Less than 20% of the circulating metronidazole is bound to plasma proteins. Metronidazole also appears in cerebrospinal fluid, saliva, and breast milk in concentration similar to those found in plasma.

Metabolism and Excretion

The average elimination half-life of metronidazole in normal volunteers is 8 hours. The major route of elimination of metronidazole and its metabolites is via the urine (60% to 80% of the dose), with fecal excretion accounting for 6% to 15% of the dose. The metabolites that appear in the urine result primarily from side-chain oxidation [1-(β-hydroxyethyl) 2-hydroxymethyl-5-nitroimidazole and 2-methyl-5-nitroimidazole-1-yl-acetic acid] and glucuronide conjugation, with unchanged metronidazole accounting for approximately 20% of the total. Renal clearance of metronidazole is approximately 10 mL/min/1.73m^2.

Decreased renal function does not alter the single dose pharmacokinetics of metronidazole. In patients with decreased liver function, plasma clearance of metronidazole is decreased.

Tetracycline Hydrochloride

Absorption, Distribution, Metabolism and Excretion

Tetracycline hydrochloride is absorbed (60%-90%) in the stomach and upper small intestine. The presence of food, milk or cations may significantly decrease the extent of absorption. In the plasma, tetracycline is bound to plasma proteins in varying degrees. It is concentrated by the liver in the bile and excreted in the urine and feces at high concentrations in biologically active form.

Tetracycline hydrochloride is distributed into most body tissues and fluids. It is distributed into the bile and undergoes varying degrees of enterohepatic recirculation. Tetracycline hydrochloride tends to localize in tumors, necrotic or ischemic tissue, liver and spleen and form tetracycline-calcium orthophosphate complexes at sites of new bone formation or tooth development. Tetracycline readily crosses the placenta and is excreted in high amounts in breast milk.

PYLERA Capsules

A comparative bioavailability study of metronidazole (375 mg), tetracycline hydrochloride (375 mg) and bismuth subcitrate potassium (420 mg, equivalent to 120 mg Bi2O3) administered as PYLERA or as 3 separate capsule formulations administered simultaneously was conducted in healthy male volunteers. The pharmacokinetic parameters for the individual drugs, when administered as separate capsule formulations or as PYLERA, are similar as shown in Table 3.

Table 3: Mean (%CV) Pharmacokinetic Parameters for Metronidazole, Tetracycline hydrochloride, and Bismuth Subcitrate Potassium in Healthy Volunteers (N=18)
 |  | Cmax (ng/mL) (%C.V.**) | AUCT (ng · h/mL) (%C.V.**) | AUC∞ (ng · h/mL) (%C.V.**)
Metronidazole | Metronidazole Capsule | 9044 (20) | 80289 (15) | 81849 (16)
 | PYLERA* | 8666.3 (22) | 83018 (17) | 84413 (17)
Tetracycline | Tetracycline Capsules | 748.0 (40) | 9544 (55) | 9864 (53)
 | PYLERA* | 774 (47) | 9674 (50) | 9987 (49)
Bismuth | Bismuth Capsule | 22 (123) | 47 (129) | 65.4 (113)
 | PYLERA* | 17 (202) | 43 (191) | 57 (178)

*PYLERA given as a single dose of 3 capsules
**C.V. Coefficient Variation

Effect of Bismuth on the Bioavailability of Tetracycline Hydrochloride

There is an anticipated reduction in tetracycline hydrochloride systemic absorption due to an interaction with bismuth. The effect of a reduced tetracycline hydrochloride systemic exposure, due to an interaction with bismuth, on the clinical efficacy of PYLERA is not thought to be clinically meaningful as the contribution of systemic, as compared to local, antimicrobial activity against Helicobacter pylori has not been established.

Effect of Food on the Bioavailability of PYLERA

The pharmacokinetic parameters for metronidazole, tetracycline hydrochloride and bismuth were also determined when PYLERA was administered under fasting and fed conditions, as shown in Table 4. Food reduced the systemic absorption of all three PYLERA components, with AUC values for metronidazole, tetracycline hydrochloride and bismuth being reduced by 6%, 34% and 60%, respectively. Reduction in the absorption of all three PYLERA components in the presence of food is not considered to be clinically significant. PYLERA should be given after meals and at bedtime, in combination with omeprazole twice a day.

Table 4: Mean PYLERA Pharmacokinetic Parameters in Fasted and Fed States (N=18)*
 | FED |  |  | FASTED
 | metronidazole | tetracycline | bismuth | metronidazole | tetracycline | bismuth
Cmax (ng/mL) (%C.V.) | 6835.0 (13) | 515.8 (36) | 1.7 (61) | 8666.3 (22) | 773.8 (47) | 16.7 (202)
Tmax (hours)** (range) | 3.0 (1.3 – 4.0) | 4.0 (2.5 – 5.0) | 3.5 (0.8 – 6.0) | 0.75 (0.5 – 3.5) | 3.3 (1.3 – 5.0) | 0.6 (0.5 – 1.7)
AUC∞ (ng · h/mL) (%C.V.) | 79225.6 (18) | 5840.1 (312) | 18.4 (116) | 84413.6 (17) | 9986.7 (49) | 56.5 (178)

*PYLERA given as a single dose of 3 capsules
**Tmax is expressed as median (range)

Effect of Omeprazole on the Bioavailability of Bismuth

The effect of omeprazole on bismuth absorption was assessed in 34 healthy volunteers given PYLERA (four times daily) with or without omeprazole (20 mg twice daily) for 6 days. In the presence of omeprazole, the extent of absorption of bismuth from PYLERA was significantly increased, compared to when no omeprazole was given (Table 5). Concentration-dependent neurotoxicity is associated with long-term use of bismuth and not likely to occur with short-term administration or at steady state concentrations below 50 ng/mL. One subject transiently achieved a maximum bismuth concentration (Cmax) higher than 50 ng/mL (73 ng/mL) following multiple dosing of PYLERA with omeprazole. The patient did not exhibit symptoms of neurotoxicity during the study. There is no clinical evidence to suggest that short-term exposure to bismuth Cmax concentrations above 50 ng/mL is associated with neurotoxicity.

Table 5: Mean Bismuth Pharmacokinetic Parameters following PYLERA Administration* With and Without Omeprazole (N=34)
Parameter | Without omeprazole |  | With omeprazole
Parameter | Mean | %C.V.** | Mean | %C.V.**
Cmax (ng/mL) | 8.1 | 84 | 25.5 | 69
AUCT (ng · h/mL) | 48.5 | 28 | 140.9 | 42

*PYLERA given as 3 capsules four times daily for 6 days with or without 20 mg omeprazole twice daily
**C.V. – Coefficient Variation

12.4 Microbiology

Mechanism of Action

PYLERA is a combination of antibacterial agents (metronidazole and tetracycline hydrochloride) and bismuth subcitrate potassium. Tetracycline hydrochloride interacts with the 30S subunit of the bacterial ribosome and inhibits protein synthesis. Metronidazole’s antibacterial mechanism of action in an anaerobic environment is not fully understood but a possible mechanism includes reduction by intracellular electron transport proteins after entry into the organism. Because of this alteration to the metronidazole molecule, a concentration gradient is created and maintained which promotes the drug’s intracellular transport. Presumably, free radicals are formed which, in turn, react with cellular components resulting in death of bacteria. The antibacterial action of bismuth salts is not well understood.

Antimicrobial Activity

PYLERA plus omeprazole therapy has been shown to be active against most isolates of Helicobacter pylori both in vitro and in clinical infections [see Clinical Studies (14)].

Susceptibility Testing

For specific information regarding susceptibility test interpretive criteria and associated test methods and quality control standards recognized by FDA for this drug, please see: https://www.fda.gov/STIC.

13 NONCLINICAL TOXICOLOGY

13.1 Carcinogenesis, Mutagenesis, Impairment of Fertility

No long-term studies have been performed to evaluate the effect of PYLERA on carcinogenesis, mutagenesis, or impairment of fertility.

Bismuth Subcitrate Potassium

No carcinogenicity or reproductive toxicity studies have been conducted with bismuth subcitrate potassium. Bismuth subsalicylate did not show mutagenic potential in the NTP Salmonella plate assay.

Metronidazole

Metronidazole has shown evidence of carcinogenic activity in a number of studies involving chronic, oral administration in mice and rats. Prominent among the effects in the mouse was an increased incidence of pulmonary tumorigenesis. This has been observed in all six reported studies in that species, including one study in which the animals were dosed on an intermittent schedule (administration during every fourth week only). At the highest dose levels, (approximately 500 mg/kg/day, which is approximately 1.6 times the indicated human dose for a 60 kg adult based on body surface area) there was a statistically significant increase in the incidence of malignant liver tumors in male mice. Also, the published results of one of the mouse studies indicate an increase in the incidence of malignant lymphomas as well as pulmonary neoplasms associated with lifetime feeding of the drug. All these effects are statistically significant. Long-term, oral-dosing studies in the rat showed statistically significant increases in the incidence of various neoplasms, particularly in mammary and hepatic tumors, among female rats administered metronidazole over those noted in the concurrent female control groups. Two lifetime tumorigenicity studies in hamsters have been performed and reported to be negative. Although metronidazole has shown mutagenic activity in a number of in vitro assay systems, studies in mammals (in vivo) have failed to demonstrate a potential for genetic damage.

Fertility studies have been conducted with male rats and mice with divergent results. Metronidazole, at doses up to 400 mg/kg/day (approximately 3 times the indicated human dose based on mg/m^2) for 28 days, failed to produce any adverse effects on fertility and testicular function in male rats. Rats treated with up to 400 mg/kg/day for 6 weeks or longer, showed severe degeneration of the seminiferous epithelium in the testes which was associated with a marked decrease in testicular spermatid counts and epididymal sperm counts and a marked decrease in fecundity. These effects were partially reversible.

Fertility studies have been performed in male mice at doses up to six times the maximum recommended human dose based upon mg/m^2 and have revealed no evidence of impaired fertility. Another fertility study was performed in male mice at oral doses of 500 mg/kg/day (approximately 2 times the indicated human dose based on mg/m²) for 14 days. Metronidazole significantly decreased testes and epididymides weight, decreased sperm viability, and increased the incidence of abnormal sperm. The viability of sperm was normal by 2 months after the start of the treatment.

Tumors affecting the liver, lungs, mammary, and lymphatic tissues have been detected in several studies of metronidazole in rats and mice, but not hamsters.

Pulmonary tumors have been observed in all six reported studies in the mouse, including one study in which the animals were dosed on an intermittent schedule (administration during every fourth week only). Malignant liver tumors were increased in male mice treated at approximately 1500 mg/m^2 (similar to the maximum recommended daily dose, based on body surface area comparisons). Malignant lymphomas and pulmonary neoplasms were also increased with lifetime feeding of the drug to mice. Mammary and hepatic tumors were increased among female rats administered oral metronidazole compared to concurrent controls. Two lifetime tumorigenicity studies in hamsters have been performed and reported to be negative.

Metronidazole has shown mutagenic activity in in vitro assay systems including the Ames test. Studies in mammals in vivo have failed to demonstrate a potential for genetic damage.

Tetracycline hydrochloride

There has been no evidence of carcinogenicity for tetracycline hydrochloride in studies conducted with rats and mice. Some related antibiotics (oxytetracycline, minocycline) have shown evidence of oncogenic activity in rats.

There was evidence of mutagenicity by tetracycline hydrochloride in two in vitro mammalian cell assay systems (L51784y mouse lymphoma and Chinese hamster lung cells).

Tetracycline hydrochloride had no effect on fertility when administered in the diet to male and female rats at a daily intake of 25 times the human dose.

14 CLINICAL STUDIES

14.1 Eradication of Helicobacter pylori in Patients with Active Duodenal Ulcer or History of Duodenal Ulcer Disease

An open-label, parallel group, active-controlled, multicenter study in Helicobacter pylori positive patients with current duodenal ulcer or a history of duodenal ulcer disease was conducted in the United States and Canada (the North American Study).

Patients were randomized to one of the following 10-day treatment regimens:

- Three (3) PYLERA capsules four times daily, after meals and at bedtime plus 20 mg omeprazole twice a day after the morning and evening meals (OBMT).
- Clarithromycin 500 mg plus 1000 mg amoxicillin plus 20 mg omeprazole twice a day before the morning and evening meals (OAC).

H. pylori eradication rates, defined as two negative ^13C-urea breath tests performed at 4 and 8 weeks post-therapy are shown in Table 6 for OBMT and OAC. The eradication rates for both groups were found to be similar using either the Per Protocol (PP) or Modified Intent-to-Treat (MITT) populations.

Table 6: Helicobacter pylori Eradication at 8 Weeks after 10 Day Treatment Regimen Percent (%) of Patients Cured [95% Confidence Interval] (Number of Patients)
 | Treatment Group |  | Difference
 | OBMT* | OAC** c
Per Protocola | 92.5% [87.8, 97.2] (n=120) | 85.7% [76.9, 91.8] (n=126) | 6.8% [-0.9, 14.5]
Modified Intent-to-Treatb | 87.7% [82.2, 93.2] (n=138) | 83.2% [77.0, 89.5] (n=137) | 4.5% [-3.9, 12.8]

*OBMT: Omeprazole + PYLERA (bismuth subcitrate potassium / metronidazole / tetracycline hydrochloride)
**OAC: Omeprazole + amoxicillin + clarithromycin
a Patients were included in the PP analysis if they had H. pylori infection documented at baseline, defined as a positive ^13C-UBT plus histology or culture, had at least one endoscopically verified duodenal ulcer ≥ 0.3 cm at baseline or had a documented history of duodenal ulcer disease, and were not protocol violators. Additionally, if patients dropped out of the study due to an adverse event related to the study drug, they were included in the evaluable analysis as failures of therapy.
b Patients were included in the MITT analysis if they had documented H. pylori infection at baseline as defined above, and had at least one documented duodenal ulcer at baseline or had a documented history of duodenal ulcer disease, and took at least one dose of study medication. All dropouts were included as failures of therapy.
c Results for OAC treatment represent all isolates regardless of clarithromycin susceptibility. Eradication rates for clarithromycin susceptible organisms, as defined by an MIC ≤ 0.25 mcg/mL, were 94.6% and 92.1% for the PP and MITT analysis, respectively. Eradication rates for clarithromycin non-susceptible organisms, as defined by an MIC ≥ 0.5 mcg/mL, were 23.1% and 21.4% for the PP and MITT analysis, respectively.

16 HOW SUPPLIED/STORAGE AND HANDLING

PYLERA is supplied as a white opaque capsule containing 140 mg bismuth subcitrate potassium, 125 mg metronidazole, and 125 mg tetracycline hydrochloride, with “BMT” printed on the cap. PYLERA capsules are supplied as the 10-day Therapy pack containing 10 blister cards, with each card containing 12 PYLERA capsules for a total of 120 capsules. PYLERA is supplied in child-resistant blisters.

NDC Number: 61269-381-12, Blister pack of 120.

Storage

Store at controlled room temperature of 20°C to 25°C (68°F to 77°F).

17 PATIENT COUNSELING INFORMATION

Lactation

Advise the lactating women to pump and discard their milk during treatment with PYLERA and for 2 days after the therapy ends [see Use in Specific Populations (8.2)].

Hypersensitivity

Inform patients that PYLERA may cause allergic reactions and to discontinue PYLERA at the first sign of urticaria, erythematous rash, flushing, and fever or other symptoms of an allergic reaction [see Contraindications (4.6)].

Severe Cutaneous Adverse Reactions

Advise patients that PYLERA capsules may increase the risk of serious and sometimes fatal dermatologic reactions, including toxic epidermal necrolysis (TEN), Stevens- Johnson syndrome (SJS), and drug reaction with eosinophilia and systemic symptoms (DRESS). Instruct the patient to be alert for skin rash, blisters, fever or other signs and symptoms of these hypersensitivity reactions. Advise patients to stop PYLERA capsules immediately if they develop any type of rash and seek medical attention [see Warnings and Precautions (5.5)].

Central Nervous System Effects

Inform patients of the risk of central and peripheral nervous system effects with PYLERA and to discontinue PYLERA and report immediately to their health-care provider if any neurologic symptoms occur [see Warnings and Precautions (5.6)].

Photosensitivity

Avoid exposure to sun or sun lamps while taking PYLERA [see Warnings and Precautions (5.8)].

Drug Interactions

Advise patients to report to their health-care provider the use of any other medications while taking PYLERA. The administration of any of the following drugs with PYLERA may result in clinically significant adverse reactions or insufficient drug efficacies [see Contraindications (4) and Drug Interactions (7)]:

- Disulfiram
- Alcoholic Beverages, or Products Containing Propylene Glycol
- Oral Contraceptives
- Anticoagulants
- Lithium
- Antacids, Multivitamins, or Dairy Products
- Busulfan
- Cimetidine
- Phenytoin and Phenobarbital

Darkening of the Tongue and/or Stool

Inform patients that PYLERA may cause temporary and harmless darkening of the tongue and/or black stool generally reversible within several days after treatment is stopped. Stool darkening should not be confused with melena (blood in the stool) [see Warnings and Precautions (5.9)].

Dosing Information

Inform patients that each dose of PYLERA includes 3 capsules. All 3 capsules should be taken 4 times a day (after meals and at bedtime) for 10 days. One omeprazole 20 mg capsule should be taken twice a day with PYLERA after the morning and evening meal for 10 days.

If a dose is missed, advise patient not to make up the dose, but to continue the normal dosing schedule until medication is gone. Patients should not take double doses. If more than 4 doses are missed, advise the patient to contact their health-care provider [see Dosage and Administration (2)].

Administration with Fluids

Instruct patients to swallow the PYLERA capsules whole with a full glass of water (8 ounces). Ingestion of adequate amounts of fluid, particularly with the bedtime dose, is recommended to reduce the risk of esophageal irritation and ulceration by tetracycline hydrochloride [see Dosage and Administration (2)].

Antibacterial Resistance

Patients should be counseled that antibacterial drugs including PYLERA should only be used to treat bacterial infections. They do not treat viral infections (e.g., the common cold). When PYLERA is prescribed to treat a bacterial infection, patients should be told that although it is common to feel better early in the course of therapy, the medication should be taken exactly as directed. Skipping doses or not completing the full course of therapy may (1) decrease the effectiveness of the immediate treatment and (2) increase the likelihood that bacteria will develop resistance and will not be treatable by PYLERA or other antibacterial drugs in the future.

Distributed By:

H2-Pharma, LLC

Montgomery, AL 36117

PYLERA® is a registered trademark of Laboratoires Juvisé Pharmaceuticals.

V4.0USPI381

Blister Pack Label - NDC 61269-381-12

PYLERA® Capsules

3 capsules per blister

Each capsule contains: Bismuth Subcitrate Potassium 140 mg, Metronidazole 125 mg, Tetracycline HCl 125 mg

Dosage: Take 3 capsules 4 times a day: see Prescribing Information for full instructions.

Separate cards, peel paper at arrow, break foil

Distributed By: H2-Pharma, LLC

Montgomery, AL 36117

NDC 61269-381-12

PYL-USA-1785

JUVISE® pharmaceuticals

Rx Only

Lot: XXXXXXX

Exp Date: YYYY/MM

Carton Label - NDC 61269-381-12

NDC 61269-381-12

120 Capsules in 10 blister cards

Each card contains 4 blisters.

Each blister contains 3 capsules.

PYLERA® CAPSULES

(bismuth subcitrate potassium 140 mg, metronidazole 125 mg, tetracycline HCl 125 mg)

10 Day Therapy PAK

Rx only

Combination therapy indicated for the eradication of Helicobacter pylori

One blister card = 1 day of therapy

JUVISE® pharmaceuticals

Distributed by: H2-Pharma, LLC

Montgomery, AL 36117

PYLERA® is a registered trademark of Laboratoires Juvisé Pharmaceuticals.

Made in France.

PYLERA® is supplied as a white opaque capsule with BMT printed on cap.

Combination therapy indicated for the treatment of patients with Helicobacter pylori infection and duodenal ulcer disease (active or history of within the past 5 years) to eradicate H. pylori

PYL-USA-1783

Daily Dosing Schedule:

Time of Dose | Number of capsules of PYLERA® | Number of capsules of omeprazole 20 mg*
After morning meal | 3 | 1
After lunch | 3 | 0
After evening meal | 3 | 1
At bedtime | 3 | 0

Each PYLERA® Capsule contains bismuth subcitrate potassium 140 mg, metronidazole 125 mg, and tetracycline hydrochloride 125 mg and the following inactive ingredients: Magnesium Stearate NF, Lactose Monohydrate NF, Talc USP, Gelatin USP, and Titanium Dioxide NF.
PYLERA® is supplied as a white opaque capsule with BMT printed on cap.

*PYLERA® Capsules do not contain omeprazole.

Store at controlled room temperature of 20°C to 25°C (68°F to 77°F).

Please see complete Prescribing Information including safety and warnings inside the box.

GTIN:

SN:

Lot No:

Exp: YYYY/MM

Datamatrix 2D